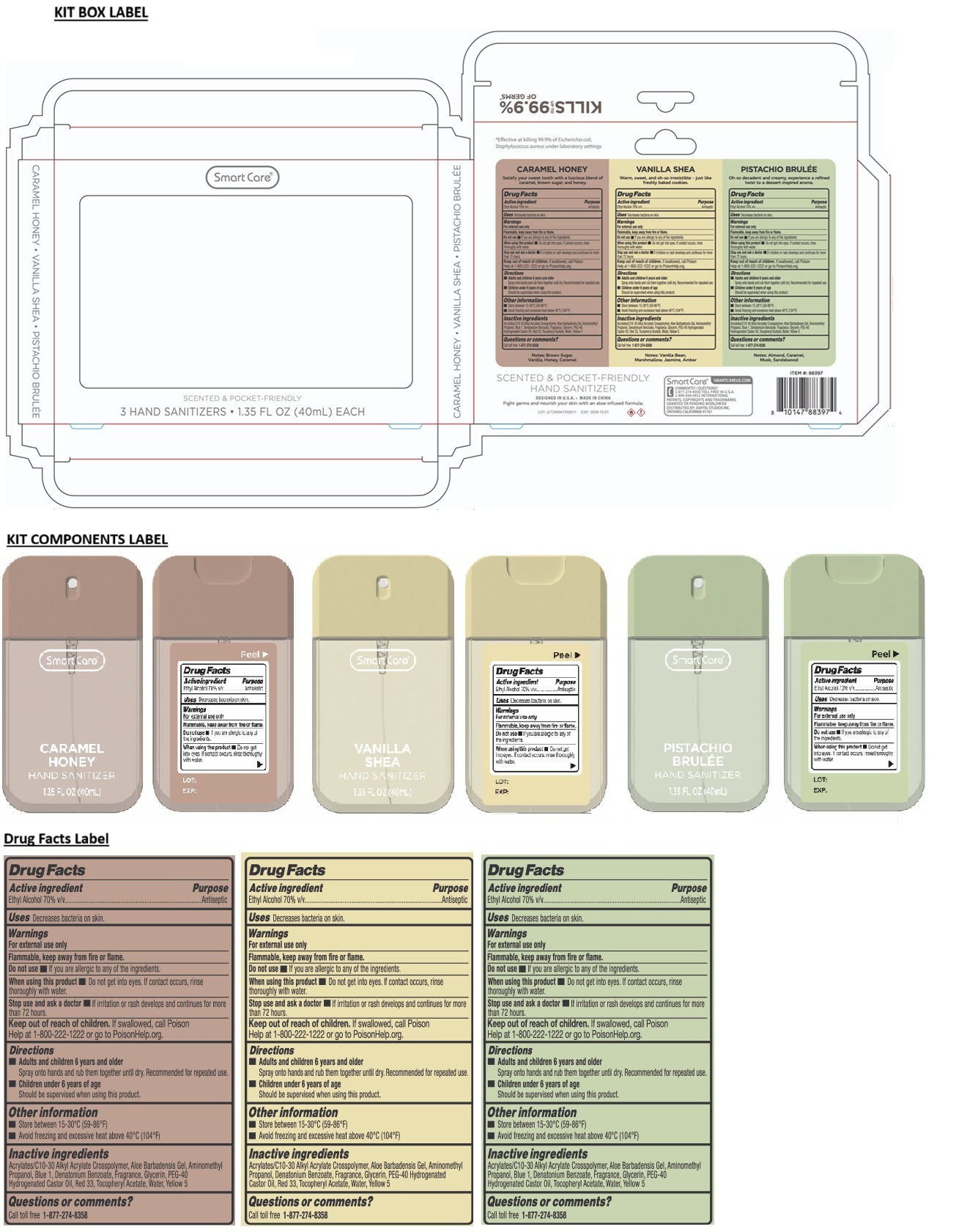 DRUG LABEL: Smart Care 3 HAND SANITIZERS 1.35 FL OZ (CARAMEL HONEY, VANILLA SHEA, PISTACHIO BRULEE)
NDC: 70108-268 | Form: KIT | Route: TOPICAL
Manufacturer: Ashtel Studios, Inc.
Category: otc | Type: HUMAN OTC DRUG LABEL
Date: 20251126

ACTIVE INGREDIENTS: ALCOHOL 70 mL/100 mL; ALCOHOL 70 mL/100 mL; ALCOHOL 100 mL/100 mL
INACTIVE INGREDIENTS: ACRYLATES/C10-30 ALKYL ACRYLATE CROSSPOLYMER (60000 MPA.S); ALOE VERA LEAF; AMINOMETHYLPROPANOL; FD&C BLUE NO. 1; DENATONIUM BENZOATE; GLYCERIN; POLYOXYL 40 HYDROGENATED CASTOR OIL; D&C RED NO. 33; .ALPHA.-TOCOPHEROL ACETATE; WATER; FD&C YELLOW NO. 5; ACRYLATES/C10-30 ALKYL ACRYLATE CROSSPOLYMER (60000 MPA.S); ALOE VERA LEAF; AMINOMETHYLPROPANOL; DENATONIUM BENZOATE; GLYCERIN; POLYOXYL 40 HYDROGENATED CASTOR OIL; D&C RED NO. 33; .ALPHA.-TOCOPHEROL ACETATE; WATER; FD&C YELLOW NO. 5; ACRYLATES/C10-30 ALKYL ACRYLATE CROSSPOLYMER (60000 MPA.S); ALOE VERA LEAF; AMINOMETHYLPROPANOL; FD&C BLUE NO. 1; DENATONIUM BENZOATE; GLYCERIN; POLYOXYL 40 HYDROGENATED CASTOR OIL; .ALPHA.-TOCOPHEROL ACETATE; WATER; FD&C YELLOW NO. 5

Smart Care® 3 HAND SANITIZERS 1.35 FL OZ (CARAMEL HONEY, VANILLA SHEA, PISTACHIO BRULEE)

Active ingredient

Ethyl Alcohol 70% v/v

Purpose

Antiseptic

Uses

Decreases bacteria on skin.

Warnings

For external use only

Flammable, keep away from fire or flame.

Do not use • If you are allergic to any of the ingredients.

When using this product • Do not get into eyes. If contact occurs, rinse thoroughly with water.

Stop use and ask a doctor • If irritation or rash develops and continues for more than 72 hours.

Keep out of reach of children. If swallowed, call Poison Help at 1-800-222-1222 or go to PoisonHelp.org.

Directions

• Adults and children 6 years and older
Spray onto hands and rub them together until dry. Recommended for repeated use.

• Children under 6 years of age
Should be supervised when using this product.

Other information

• Store between 15-30°C (59-86°F)
• Avoid freezing and excessive heat above 40°C (104°F)

Inactive ingredients

Acrylates/C10-30 Alkyl Acrylates Crosspolymer, Aloe Barbadensis Gel, Aminomethyl Propanol, Blue 1, Denatonium Benzoate, Fragrance, Glycerin, PEG-40 Hydrogenated Castor Oil, Red 33, Tocopheryl Acetate, Water, Yellow 5

Questions or comments?

Call toll free 1-877-274-8358

Active ingredient

Ethyl Alcohol 70% v/v

Purpose

Antiseptic

Uses

Decreases bacteria on skin.

Warnings

For external use only

Flammable, keep away from fire or flame.

Do not use • If you are allergic to any of the ingredients.

When using this product • Do not get into eyes. If contact occurs, rinse thoroughly with water.

Stop use and ask a doctor • If irritation or rash develops and continues for more than 72 hours.

Keep out of reach of children. If swallowed, call Poison Help at 1-800-222-1222 or go to PoisonHelp.org.

Directions

• Adults and children 6 years and older
Spray onto hands and rub them together until dry. Recommended for repeated use.

• Children under 6 years of age
Should be supervised when using this product.

Other information

• Store between 15-30°C (59-86°F)
• Avoid freezing and excessive heat above 40°C (104°F)

Inactive ingredients

Acrylates/C10-30 Alkyl Acrylates Crosspolymer, Aloe Barbadensis Gel, Aminomethyl Propanol, Denatonium Benzoate, Fragrance, Glycerin, PEG-40 Hydrogenated Castor Oil, Red 33, Tocopheryl Acetate, Water, Yellow 5

Questions or comments?

Call toll free 1-877-274-8358

Active ingredient

Ethyl Alcohol 70% v/v

Purpose

Antiseptic

Uses

Decreases bacteria on skin.

Warnings

For external use only

Flammable, keep away from fire or flame.

Do not use • If you are allergic to any of the ingredients.

When using this product • Do not get into eyes. If contact occurs, rinse thoroughly with water.

Stop use and ask a doctor • If irritation or rash develops and continues for more than 72 hours.

Keep out of reach of children. If swallowed, call Poison Help at 1-800-222-1222 or go to PoisonHelp.org.

Directions

• Adults and children 6 years and older
Spray onto hands and rub them together until dry. Recommended for repeated use.

• Children under 6 years of age
Should be supervised when using this product.

Other information

• Store between 15-30°C (59-86°F)
• Avoid freezing and excessive heat above 40°C (104°F)

Inactive ingredients

Acrylates/C10-30 Alkyl Acrylates Crosspolymer, Aloe Barbadensis Gel, Aminomethyl Propanol, Blue 1, Denatonium Benzoate, Fragrance, Glycerin, PEG-40 Hydrogenated Castor Oil, Tocopheryl Acetate, Water, Yellow 5

Questions or comments?

Call toll free 1-877-274-8358

SCENTED & POCKET-FRIENDLY

*Effective at killing 99.9% of Escherichia coli, Staphylococcus aureus under laboratory settings

CARAMEL HONEY
Satisfy your sweet tooth with a luscious blend of caramel, brown sugar, and honey.

Notes: Brown Sugar, Vanilla, Honey, Caramel

VANILLA SHEA
Warm, sweet, and oh-so irresistible - just like freshly baked cookies.

Notes: Vanilla Bean, Marshmallow, Jasmine, Amber

PISTACHIO BRULEE
Oh-so decadent and creamy, experience a refined twist to a dessert-inspired aroma.

Note: Almond, Caramel, Musk, Sandalwood

Designed in U.S.A. • MADE IN CHINA

Fight germs and nourish your skin with an aloe-infused formula.

Smart Care®
SMARTCAREUS.COM

1-909-434-0911 INTERNATIONAL

PATENTS, COPYRIGHTS AND TRADEMARKS GRANTED OR PENDING WORLDWIDE

DISTRIBUTED BY: ASHTEL STUDIOS, INC.
ONTARIO, CALIFORNIA 91761

KILLS UP TO 99.9% OF GERMS*